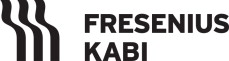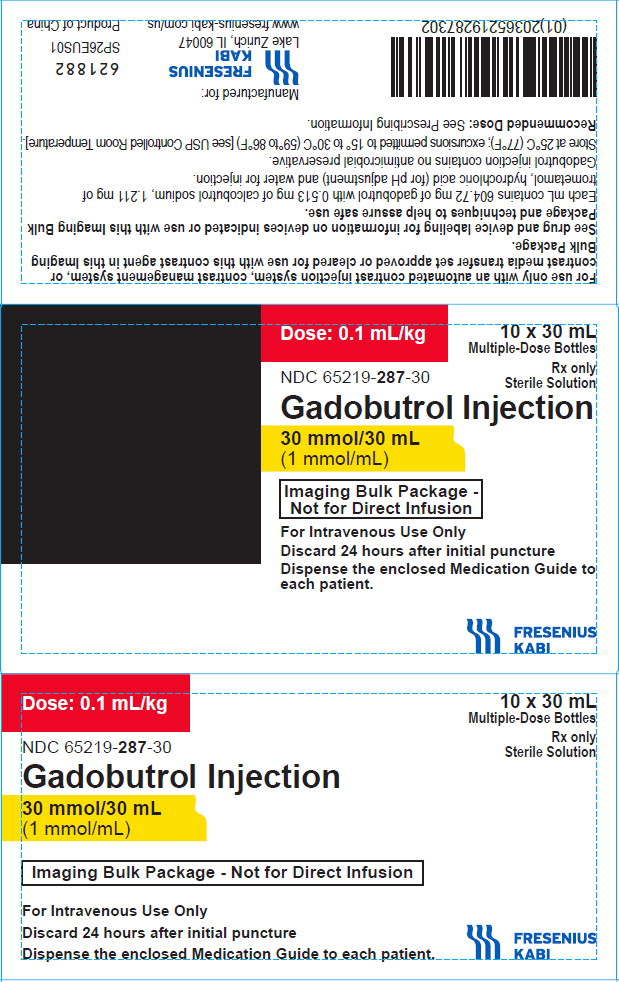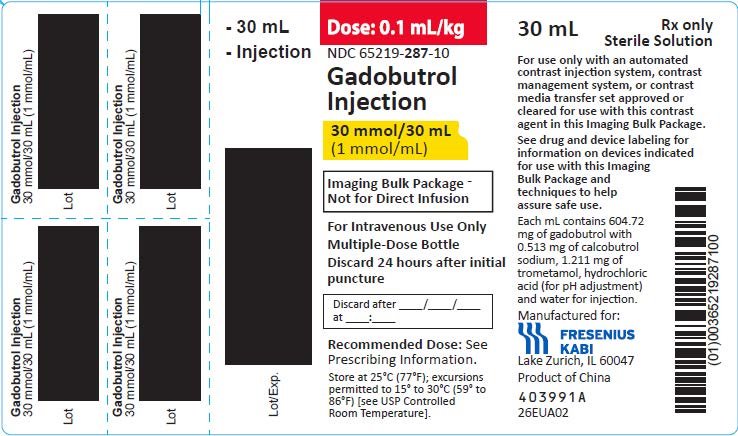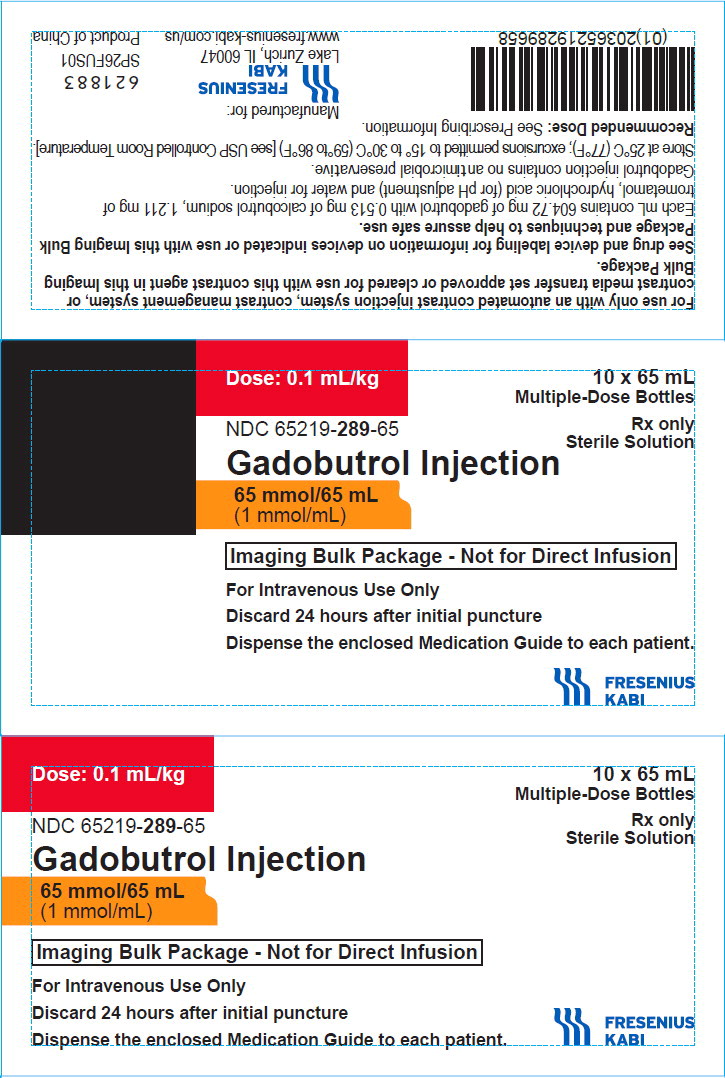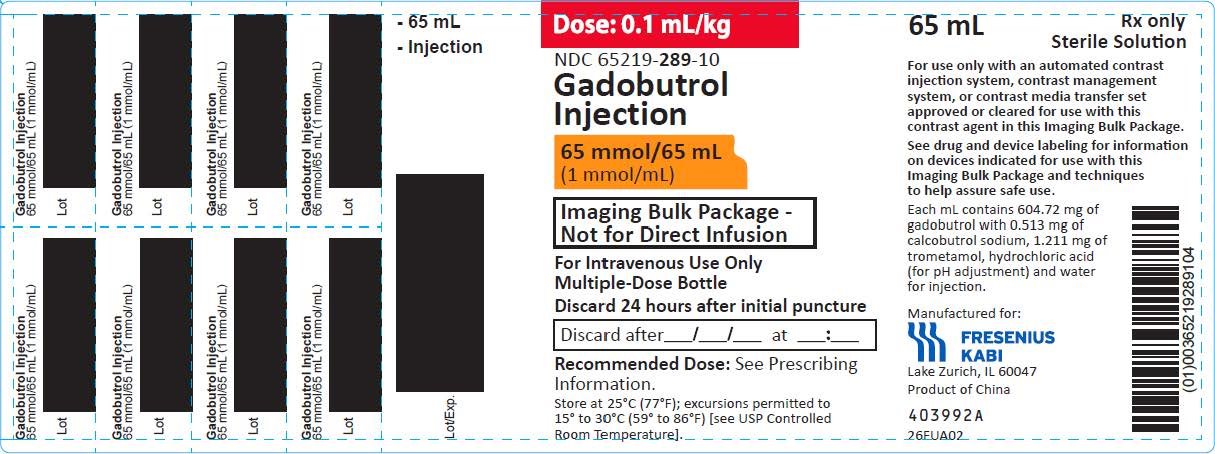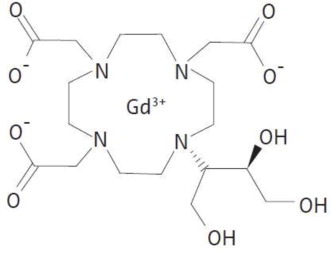 DRUG LABEL: Gadobutrol
NDC: 65219-287 | Form: INJECTION
Manufacturer: Fresenius Kabi USA, LLC
Category: prescription | Type: HUMAN PRESCRIPTION DRUG LABEL
Date: 20251031

ACTIVE INGREDIENTS: Gadobutrol 604.72 mg/1 mL
INACTIVE INGREDIENTS: Tromethamine; Calcobutrol Sodium; Hydrochloric Acid; Water

HIGHLIGHTS OF PRESCRIBING INFORMATION

These highlights do not include all the information needed to use GADOBUTROL INJECTION safely and effectively. See full prescribing information for GADOBUTROL INJECTION.
GADOBUTROL injection, for intravenous use
Initial U.S. Approval: 2011
IMAGING BULK PACKAGE
NOT FOR DIRECT INFUSION

RECENT MAJOR CHANGES

Warnings and Precautions,
Acute Respiratory Distress Syndrome (5.4) 3/2025

WARNING: RISK ASSOCIATED WITH INTRATHECAL USE and NEPHROGENIC SYSTEMIC FIBROSIS

See full prescribing information for complete boxed warning

- Intrathecal administration of gadolinium-based contrast agents (GBCAs) can cause serious adverse reactions including death, coma, encephalopathy, and seizures. Gadobutrol injection is not approved for intrathecal use (5.1)
- GBCAs increase the risk for nephrogenic systemic fibrosis (NSF) among patients with impaired elimination of the drugs. Avoid use of gadobutrol injection in these patients unless the diagnostic information is essential and not available with non-contrasted MRI or other modalities.
  The risk for NSF appears highest among patients with: Screen patients for acute kidney injury and other conditions that may reduce renal function. For patients at risk for chronically reduced renal function (for example, age >60 years, hypertension or diabetes), estimate the glomerular filtration rate (GFR) through laboratory testing (5.2).
  - Chronic, severe kidney disease (GFR < 30 mL/min/1.73m^2), or
  - Acute kidney injury.

Screen patients for acute kidney injury and other conditions that may reduce renal function. For patients at risk for chronically reduced renal function (for example, age >60 years, hypertension or diabetes), estimate the glomerular filtration rate (GFR) through laboratory testing (5.2)

1 INDICATIONS AND USAGE

Gadobutrol injection is a gadolinium-based contrast agent indicated for use with magnetic resonance imaging (MRI):

- To detect and visualize areas with disrupted blood brain barrier and/or abnormal vascularity of the central nervous system in adult and pediatric patients (including term neonates) (1.1)
- To assess the presence and extent of malignant breast disease in adult patients (1.2)
- To evaluate known or suspected supra-aortic or renal artery disease in adult and pediatric patients (including term neonates) (1.3)
- To assess myocardial perfusion (stress, rest) and late gadolinium enhancement in adult patients with known or suspected coronary artery disease (CAD). (1.4).

2 DOSAGE AND ADMINISTRATION

- Recommended dose for adults and pediatric patients (including term neonates) is 0.1 mL/kg body weight (2.1)
- Administer as an intravenous bolus injection (2.2)
- Follow injection with a normal saline flush (2.2)

3 DOSAGE FORMS AND STRENGTHS

Gadobutrol injection contains 604.72 mg gadobutrol/mL (equivalent to 1 mmol gadobutrol/mL) (3)

4 CONTRAINDICATIONS

History of severe hypersensitivity reaction to gadobutrol (4)

5 WARNINGS AND PRECAUTIONS

- Hypersensitivity Reactions: Anaphylactic and other hypersensitivity reactions with cardiovascular, respiratory or cutaneous manifestations, ranging from mild to severe, including death, have occurred. Monitor patients closely during and after administration of gadobutrol. (5.3)
- Acute Respiratory Distress Syndrome: For patients demonstrating respiratory distress after administration, assess oxygen requirement and monitor for worsening respiratory function. (5.4)
- Gadolinium Retention: Gadolinium is retained for months or years in brain, bone, and other organs. (5.5)

6 ADVERSE REACTIONS

Most common adverse reactions (incidence ≥ 0.5%) are headache, nausea, and dizziness (6.1)

To report SUSPECTED ADVERSE REACTIONS, contact Fresenius Kabi USA, LLC at 1-800-551-7176 or FDA at 1-800-FDA-1088 or www.fda.gov/medwatch

8 USE IN SPECIFIC POPULATIONS

Pregnancy: Use only if imaging is essential during pregnancy and cannot be delayed. (8.1)

FULL PRESCRIBING INFORMATION

WARNING: RISK ASSOCIATED WITH INTRATHECAL USE and NEPHROGENIC SYSTEMIC FIBROSIS

Risk Associated with Intrathecal Use
Intrathecal administration of gadolinium-based contrast agents (GBCAs) can cause serious adverse reactions including death, coma, encephalopathy, and seizures. Gadobutrol injection is not approved for intrathecal use [see Warnings and Precautions (5.1)].

Nephrogenic Systemic Fibrosis
GBCAs increase the risk for nephrogenic systemic fibrosis (NSF) among patients with impaired elimination of drugs. Avoid use of gadobutrol injection in these patients unless the diagnostic information is essential and not available with non-contrasted MRI or other modalities. NSF may result in fatal or debilitating fibrosis affecting the skin, muscle and internal organs.

- The risk for NSF appears highest among patients with:
  - Chronic, severe kidney disease (GFR < 30 mL/min/1.73m^2), or
  - Acute kidney injury.
- Screen patients for acute kidney injury and other conditions that may reduce renal function. For patients at risk for chronically reduced renal function (for example, age > 60 years, hypertension or diabetes), estimate the glomerular filtration rate (GFR) through laboratory testing.
- For patients at highest risk for NSF, do not exceed the recommended gadobutrol dose and allow a sufficient period of time for elimination of the drug from the body prior to any re-administration [see Warnings and Precautions (5.2)].

1 INDICATIONS AND USAGE

1.1 Magnetic Resonance Imaging (MRI) of the Central Nervous System (CNS)

Gadobutrol injection is indicated for use with magnetic resonance imaging (MRI) in adult and pediatric patients, including term neonates, to detect and visualize areas with disrupted blood brain barrier and/or abnormal vascularity of the central nervous system.

1.2 MRI of the Breast

Gadobutrol injection is indicated for use with MRI in adult patients to assess the presence and extent of malignant breast disease.

1.3 Magnetic Resonance Angiography (MRA)

Gadobutrol injection is indicated for use in magnetic resonance angiography (MRA) in adult and pediatric patients, including term neonates, to evaluate known or suspected supra-aortic or renal artery disease.

1.4 Cardiac MRI

Gadobutrol injection is indicated for use in cardiac MRI (CMRI) to assess myocardial perfusion (stress, rest) and late gadolinium enhancement in adult patients with known or suspected coronary artery disease (CAD).

2 DOSAGE AND ADMINISTRATION

2.1 Recommended Dose

The recommended dose of gadobutrol injection for adult and pediatric patients (including term neonates) is 0.1 mL/kg body weight (0.1 mmol/kg). Refer to Table 1 to determine the volume to be administered.

Table 1: Volume of Gadobutrol Injection by Body Weight
Body Weight (kg) | Volume to be Administered (mL)
2.5 | 0.25
5 | 0.5
10 | 1
15 | 1.5
20 | 2
25 | 2.5
30 | 3
35 | 3.5
40 | 4
45 | 4.5
50 | 5
60 | 6
70 | 7
80 | 8
90 | 9
100 | 10
110 | 11
120 | 12
130 | 13
140 | 14
*For Cardiac MRI, the dose is divided into 2 separate, equal injections

2.2 Administration Guidelines

Gadobutrol injection is formulated at a higher concentration (1 mmol/mL) compared to certain other gadolinium based contrast agents, resulting in a lower volume of administration. Use Table 1 to determine the volume to be administered.

Use sterile technique when preparing and administering gadobutrol injection.

MRI of the Central Nervous System

- Administer gadobutrol injection as an intravenous injection, manually or by power injector, at a flow rate of approximately 2 mL/second.
- Follow gadobutrol injection with flush of 0.9% Sodium Chloride Injection, USP to ensure complete administration of the contrast.
- Post contrast MRI can commence immediately following contrast administration.

MRI of the Breast

- Administer gadobutrol injection as an intravenous bolus by power injector, followed by a flush of 0.9% Sodium Chloride Injection, USP to ensure complete administration of the contrast.
- Start image acquisition following contrast administration and then repeat sequentially to determine peak intensity and wash-out.

MR Angiography

Image acquisition should coincide with peak arterial concentration, which varies among patients.

Adults

- Administer gadobutrol injection by power injector, at a flow rate of approximately 1.5 mL/second, followed by a 30 mL flush of 0.9% Sodium Chloride Injection, USP at the same rate to ensure complete administration of the contrast.

Pediatric patients

- Administer gadobutrol injection by power injector or manually, followed by a flush of 0.9% Sodium Chloride Injection, USP to ensure complete administration of the contrast.

Cardiac MRI

- Administer gadobutrol injection through a separate intravenous line in the contralateral arm if concomitantly providing a continuous infusion of a pharmacologic stress agent.
- Administer gadobutrol injection as two (2) separate bolus injections: 0.05 mL/kg (0.05 mmol/kg) body weight at peak pharmacologic stress followed by 0.05 mL/kg (0.05 mmol/kg) body weight at rest.
- Administer gadobutrol injection via a power injector at a flow rate of approximately 4 mL/second and follow each injection with a flush of 20 mL of 0.9% Sodium Chloride Injection, USP at the same flow rate.

2.3 Drug Handling

- Visually inspect gadobutrol injection for particulate matter and discoloration prior to administration. Do not use the solution if it is discolored, if particulate matter is present or if the container appears damaged.
- Do not mix gadobutrol injection with other medications and do not administer gadobutrol injection in the same intravenous line simultaneously with other medications because of the potential for chemical incompatibility.
- Instructions of the device manufacturer must be followed.

2.4 Imaging Bulk Package Preparation Instructions

Gadobutrol injection Imaging Bulk Package (IBP) is a container of a sterile preparation for parenteral use that contains many single doses of gadobutrol for use with a medical imaging device. Gadobutrol injection Imaging Bulk Package is for intravenous use and not for direct infusion. Gadobutrol injection Imaging Bulk Package is for use only with an automated contrast injection system, contrast management system, or contrast media transfer set approved or cleared for use with this contrast agent in this Imaging Bulk Package. Please see drug and device labeling for information on devices indicated for use with this Imaging Bulk Package and techniques to help assure safe use.

1. The Gadobutrol injection Imaging Bulk Package is to be used only in a room designated for radiological procedures that involve intravascular administration of a contrast agent.
2. Utilize aseptic technique for penetrating the container closure of the Gadobutrol injection Imaging Bulk Package and transferring Gadobutrol injection.
3. The container closure must be penetrated only one time with a suitable sterile component of the automated contrast injection system, contrast management system, or contrast media transfer set (e.g., transfer spike) approved or cleared for use with this contrast agent in this Imaging Bulk Package.
4. Once the Gadobutrol injection Imaging Bulk Package is punctured, do not remove it from the work area during the entire period of use. Storage temperature of Gadobutrol injection Imaging Bulk Package after the closure has been entered is 20°C to 25°C (68°F to 77°F).
5. A maximum use time of 24 hours from initial puncture is permitted to complete fluid transfer. Discard any unused Gadobutrol injection 24 hours after initial puncture of the Imaging Bulk Package.
6. After the container closure is punctured, if the integrity of the Imaging Bulk Package and the delivery system cannot be assured through direct continuous supervision, the Imaging Bulk Package and all associated disposables for the automated contrast injection system, contrast management system, or contrast media transfer set (e.g., transfer spike) should be discarded.

3 DOSAGE FORMS AND STRENGTHS

Gadobutrol injection is a sterile, clear, and colorless to pale yellow solution for injection containing 604.72 mg gadobutrol per mL (equivalent to 1 mmol gadobutrol/mL).

4 CONTRAINDICATIONS

Gadobutrol injection is contraindicated in patients with history of severe hypersensitivity reactions to gadobutrol.

5 WARNINGS AND PRECAUTIONS

5.1 Risk Associated with Intrathecal Use

Intrathecal administration of GBCAs can cause serious adverse reactions including death, coma, encephalopathy, and seizures. The safety and effectiveness of Gadobutrol injection have not been established with intrathecal use. Gadobutrol injection is not approved for intrathecal use [see Dosage and Administration (2.2)].

5.2 Nephrogenic Systemic Fibrosis

GBCAs increase the risk for nephrogenic systemic fibrosis (NSF) among patients with impaired elimination of the drugs. Avoid use of gadobutrol injection among these patients unless the diagnostic information is essential and not available with non-contrast MRI or other modalities. The GBCA-associated NSF risk appears highest for patients with chronic, severe kidney disease (GFR < 30 mL/min/1.73m^2) as well as patients with acute kidney injury. The risk appears lower for patients with chronic, moderate kidney disease (GFR 30 to 59 mL/min/1.73m^2) and little, if any, for patients with chronic, mild kidney disease (GFR 60 to 89 mL/min/1.73m^2). NSF may result in fatal or debilitating fibrosis affecting the skin, muscle and internal organs. Report any diagnosis of NSF following gadobutrol administration to Fresenius Kabi USA, LLC at 1-800-551-7176 or FDA (1-800-FDA-1088 or www.fda.gov/medwatch).

Screen patients for acute kidney injury and other conditions that may reduce renal function. Features of acute kidney injury consist of rapid (over hours to days) and usually reversible decrease in kidney function, commonly in the setting of surgery, severe infection, injury or drug-induced kidney toxicity. Serum creatinine levels and estimated GFR may not reliably assess renal function in the setting of acute kidney injury. For patients at risk for chronically reduced renal function (for example, age > 60 years, diabetes mellitus or chronic hypertension), estimate the GFR through laboratory testing.

Among the factors that may increase the risk for NSF are repeated or higher than recommended doses of a GBCA and degree of renal impairment at the time of exposure. Record the specific GBCA and the dose administered to a patient. For patients at highest risk for NSF, do not exceed the recommended gadobutrol dose and allow a sufficient period of time for elimination of the drug prior to re-administration. For patients receiving hemodialysis, consider the prompt initiation of hemodialysis following the administration of a GBCA in order to enhance the contrast agent's elimination [see Use in Specific Populations (8.6) and Clinical Pharmacology (12.3)]. The usefulness of hemodialysis in the prevention of NSF is unknown [see Clinical Pharmacology (12.3)].

5.3 Hypersensitivity Reactions

Anaphylactic and other hypersensitivity reactions with cardiovascular, respiratory or cutaneous manifestations, ranging from mild to severe, including death, have uncommonly occurred following gadobutrol administration [see Adverse Reactions (6)].

- Before gadobutrol administration, assess all patients for any history of a reaction to contrast media, bronchial asthma and/or allergic disorders. These patients may have an increased risk for a hypersensitivity reaction to gadobutrol.
- Administer gadobutrol only in situations where trained personnel and therapies are promptly available for the treatment of hypersensitivity reactions, including personnel trained in resuscitation.

Most hypersensitivity reactions to gadobutrol have occurred within half an hour after administration. Delayed reactions can occur up to several days after administration. Observe patients for signs and symptoms of hypersensitivity reactions during and following gadobutrol administration.

5.4 Acute Respiratory Distress Syndrome

Acute respiratory distress syndrome (ARDS) has been reported in patients administered gadobutrol injection and may be characterized by severe hypoxemia requiring oxygen support and mechanical ventilation. These manifestations may resemble an immediate hypersensitivity reaction with onset of respiratory distress within <30 minutes to 24 hours after gadobutrol injection administration. For patients demonstrating respiratory distress after gadobutrol injection administration, assess oxygen requirement and monitor for worsening respiratory function.

5.5 Gadolinium Retention

Gadolinium is retained for months or years in several organs. The highest concentrations (nanomoles per gram of tissue) have been identified in the bone, followed by other organs (for example, brain, skin, kidney, liver, and spleen). The duration of retention also varies by tissue and is longest in bone. Linear GBCAs cause more retention than macrocyclic GBCAs. At equivalent doses, gadolinium retention varies among the linear agents with Omniscan (gadodiamide) and Optimark (gadoversetamide) causing greater retention than other linear agents [Eovist (gadoxetate disodium), Magnevist (gadopentetate dimeglumine), MultiHance (gadobenate dimeglumine)]. Retention is lowest and similar among the macrocyclic GBCAs [Dotarem (gadoterate meglumine), Gadobutrol injection (gadobutrol), ProHance (gadoteridol)].

Consequences of gadolinium retention in the brain have not been established. Pathologic and clinical consequences of GBCA administration and retention in skin and other organs have been established in patients with impaired renal function [see Warnings and Precautions (5.2)]. There are rare reports of pathologic skin changes in patients with normal renal function. Adverse events involving multiple organ systems have been reported in patients with normal renal function without an established causal link to gadolinium retention [see Adverse Reactions (6.2)].

While clinical consequences of gadolinium retention have not been established in patients with normal renal function, certain patients might be at higher risk. These include patients requiring multiple lifetime doses, pregnant and pediatric patients, and patients with inflammatory conditions. Consider the retention characteristics of the agent when choosing a GBCA for these patients. Minimize repetitive GBCA imaging studies particularly closely spaced studies, when possible.

5.6 Acute Kidney Injury

In patients with chronic renal impairment, acute kidney injury sometimes requiring dialysis has been observed with the use of some GBCAs. Do not exceed the recommended dose; the risk of acute kidney injury may increase with higher than recommended doses.

5.7 Extravasation and Injection Site Reactions

Ensure catheter and venous patency before the injection of gadobutrol. Extravasation into tissues during gadobutrol administration may result in moderate irritation [see Nonclinical Toxicology (13.2)].

5.8 Overestimation of Extent of Malignant Disease in MRI of the Breast

Gadobutrol MRI of the breast overestimated the histologically confirmed extent of malignancy in the diseased breast in up to 50% of the patients [see Clinical Studies (14.2)].

5.9 Low Sensitivity for Significant Arterial Stenosis

The performance of gadobutrol MRA for detecting arterial segments with significant stenosis (>50% renal, >70% supra-aortic) has not been shown to exceed 55%. Therefore, a negative MRA study alone should not be used to rule out significant stenosis [see Clinical Studies (14.3)].

6 ADVERSE REACTIONS

The following clinically significant adverse reactions are discussed elsewhere in labeling:

- Nephrogenic Systemic Fibrosis (NSF) [see Boxed Warning and Warnings and Precautions (5.2)].
- Hypersensitivity reactions [see Contraindications (4) and Warnings and Precautions (5.3)].
- Acute Respiratory Distress Syndrome [see Warnings and Precautions (5.4)].
- Gadolinium Retention [see Warnings and Precautions (5.5)].

6.1 Clinical Trials Experience

Because clinical trials are conducted under widely varying conditions, adverse reaction rates observed in the clinical trials of a drug cannot be directly compared to rates in the clinical trials of another drug and may not reflect the rates observed in clinical practice.

The adverse reactions described in this section reflect gadobutrol exposure in 7713 subjects (including 184 pediatric patients, ages 0 to 17 years) with the majority receiving the recommended dose. Approximately 52% of the subjects were male and the ethnic distribution was 62% Caucasian, 28% Asian, 5% Hispanic, 2.5% Black, and 2.5% patients of other ethnic groups. The average age was 56 years (range from 1 week to 93 years).

Overall, approximately 4% of subjects reported one or more adverse reactions during a follow-up period that ranged from 24 hours to 7 days after gadobutrol administration.

Adverse reactions associated with the use of gadobutrol were usually mild to moderate in severity and transient in nature.

Table 2 lists adverse reactions that occurred in ≥ 0.1% subjects who received gadobutrol.

Table 2: Adverse Reactions
Reaction | Rate (%) n=7713
Headache | 1.7
Nausea | 1.2
Dizziness | 0.5
Dysgeusia | 0.4
Feeling Hot | 0.4
Injection site reactions | 0.4
Vomiting | 0.4
Rash (includes generalized, macular, papular, pruritic) | 0.3
Erythema | 0.2
Paresthesia | 0.2
Pruritus (includes generalized) | 0.2
Dyspnea | 0.1
Urticaria | 0.1

Adverse reactions that occurred with a frequency of < 0.1% in subjects who received gadobutrol include: hypersensitivity/anaphylactic reaction, loss of consciousness, convulsion, parosmia, tachycardia, palpitation, dry mouth, malaise and feeling cold.

6.2 Postmarketing Experience

The following additional adverse reactions have been identified during postmarketing use of gadobutrol or other GBCAs. Because these reactions are reported voluntarily from a population of uncertain size, it is not possible to reliably estimate their frequency or establish a causal relationship to drug exposure.

- Cardiac arrest
- Nephrogenic Systemic Fibrosis (NSF)
- Hypersensitivity reactions (anaphylactic shock, circulatory collapse, respiratory arrest, bronchospasm, cyanosis, oropharyngeal swelling, laryngeal edema, blood pressure increased, chest pain, angioedema, conjunctivitis, hyperhidrosis, cough, sneezing, burning sensation, and pallor).
- Respiratory, Thoracic, and Mediastinal Disorders: Acute respiratory distress syndrome, pulmonary edema
- General Disorders and Administration Site Conditions: Adverse reactions with variable onset and duration have been reported after GBCA administration. These include fatigue, asthenia, pain syndromes, and heterogeneous clusters of symptoms in the neurological, cutaneous, and musculoskeletal systems.
- Skin: Gadolinium associated plaques
- Gastrointestinal Disorders: Acute pancreatitis with onset within 48 hours after GBCA administration

8 USE IN SPECIFIC POPULATIONS

8.1 Pregnancy

Risk Summary

GBCAs cross the placenta and result in fetal exposure and gadolinium retention. The human data on the association between GBCAs and adverse fetal outcomes are limited and inconclusive (see Data). In animal reproduction studies, although teratogenicity was not observed, embryolethality was observed in monkeys, rabbits and rats receiving intravenous gadobutrol during organogenesis at doses 8 times and above the recommended human dose. Retardation of embryonal development was observed in rabbits and rats receiving intravenous gadobutrol during organogenesis at doses 8 and 12 times, respectively, the recommended human dose (see Data). Because of the potential risks of gadolinium to the fetus, use gadobutrol only if imaging is essential during pregnancy and cannot be delayed.

The estimated background risk of major birth defects and miscarriage for the indicated population is unknown. In the U.S. general population, the estimated background risk of major birth defects and miscarriage in clinically recognized pregnancies is 2% to 4% and is 15% to 20%, respectively.

Data

Human Data

Contrast enhancement is visualized in the placenta and fetal tissues after maternal GBCA administration.

Cohort studies and case reports on exposure to GBCAs during pregnancy have not reported a clear association between GBCAs and adverse effects in the exposed neonates. However, a retrospective cohort study, comparing pregnant women who had a GBCA MRI to pregnant women who did not have an MRI, reported a higher occurrence of stillbirths and neonatal deaths in the group receiving GBCA MRI. Limitations of this study include a lack of comparison with non-contrast MRI and lack of information about the maternal indication for MRI. Overall, these data preclude a reliable evaluation of the potential risk of adverse fetal outcomes with the use of GBCAs in pregnancy.

Animal Data

Gadolinium Retention

GBCAs administered to pregnant non-human primates (0.1 mmol/kg on gestational days 85 and 135) result in measurable gadolinium concentration in the offspring in bone, brain, skin, liver, kidney, and spleen for at least 7 months. GBCAs administered to pregnant mice (2 mmol/kg daily on gestational days 16 through 19) result in measurable gadolinium concentrations in the pups in bone, brain, kidney, liver, blood, muscle, and spleen at one month postnatal age.

Reproductive Toxicology

Embryolethality was observed when gadobutrol was administered intravenously to monkeys during organogenesis at doses 8 times the recommended single human dose (based on body surface area); gadobutrol was not maternally toxic or teratogenic at this dose. Embryolethality and retardation of embryonal development also occurred in pregnant rats receiving maternally toxic doses of gadobutrol (≥ 7.5 mmol/kg body weight; equivalent to 12 times the human dose based on body surface area) and in pregnant rabbits (≥ 2.5 mmol/kg body weight; equivalent to 8 times the recommended human dose based on body surface area). In rabbits, this finding occurred without evidence of pronounced maternal toxicity and with minimal placental transfer (0.01% of the administered dose detected in the fetuses).

Because pregnant animals received repeated daily doses of gadobutrol, their overall exposure was significantly higher than that achieved with the standard single dose administered to humans.

8.2 Lactation

Risk Summary

There are no data on the presence of gadobutrol in human milk, the effects on the breastfed infant, or the effects on milk production. However, published lactation data on other GBCAs indicate that 0.01% to 0.04% of the maternal gadolinium dose is present in breast milk and there is limited GBCA gastrointestinal absorption in the breast-fed infant. Gadobutrol is present in rat milk (see Data). The developmental and health benefits of breastfeeding should be considered along with the mother's clinical need for gadobutrol and any potential adverse effects on the breastfed infant from gadobutrol or from the underlying maternal condition.

Data

In lactating rats receiving 0.5 mmol/kg of intravenous [^153Gd]-gadobutrol, 0.01% of the total administered radioactivity was transferred to the pup via maternal milk within 3 hours after administration, and the gastrointestinal absorption is poor (approximately 5% of the dose orally administered was excreted in the urine).

8.4 Pediatric Use

The safety and effectiveness of gadobutrol have been established in pediatric patients, including term neonates, for use with MRI to detect and visualize areas with disrupted blood brain barrier and/or abnormal vascularity of the central nervous system and for use in MRA to evaluate known or suspected supra-aortic or renal artery disease. Use of gadobutrol in these indications is supported by adequate and well-controlled studies in adults and supportive imaging data in two studies in 135 patients 2 to less than 18 years of age and 44 patients less than 2 years of age with CNS and non-CNS lesions, and pharmacokinetic data in 130 patients 2 to less than 18 years of age and 43 patients less than 2 years of age, including term neonates [see Clinical Pharmacology (12.3) and Clinical Studies (14.1)]. The frequency, type, and severity of adverse reactions in pediatric patients were similar to adverse reactions in adults [see Adverse Reactions (6.1)]. No dose adjustment according to age is necessary in pediatric patients [see Dosage and Administration (2.1), Clinical Pharmacology (12.3), and Clinical Studies (14.1)]. The safety and effectiveness of gadobutrol have not been established in preterm neonates for any indication or in pediatric patients of any age for use with MRI to assess the presence and extent of malignant breast disease, or for use in CMRI to assess myocardial perfusion (stress, rest) and late gadolinium enhancement in patients with known or suspected coronary artery disease (CAD).

NSF Risk

No case of NSF associated with gadobutrol or any other GBCA has been identified in pediatric patients ages 6 years and younger. Pharmacokinetic studies suggest that clearance of gadobutrol is similar in pediatric patients and adults, including pediatric patients age younger than 2 years. No increased risk factor for NSF has been identified in juvenile animal studies of gadobutrol. Normal estimated GFR (eGFR) is around 30 mL/min/1.73m^2 at birth and increases to mature levels around 1 year of age, reflecting growth in both glomerular function and relative body surface area. Clinical studies in pediatric patients younger than 1 year of age have been conducted in patients with the following minimum eGFR: 31 mL/min/1.73m^2 (age 2 to 7 days), 38 mL/min/1.73m^2 (age 8 to 28 days), 62 mL/min/1.73m^2 (age 1 to 6 months), and 83 mL/min/1.73m^2 (age 6 to 12 months).

Juvenile Animal Data

Single and repeat-dose toxicity studies in neonatal and juvenile rats did not reveal findings suggestive of a specific risk for use in pediatric patients including term neonates and infants.

8.5 Geriatric Use

In clinical studies of gadobutrol, 1,377 patients were 65 years of age and over, while 104 patients were 80 years of age and over. No overall differences in safety or effectiveness were observed between these subjects and younger subjects, and other reported clinical experience has not identified differences in responses between the elderly and younger patients. In general, use of gadobutrol in elderly patients should be cautious, reflecting the greater frequency of impaired renal function and concomitant disease or other drug therapy. No dose adjustment according to age is necessary in this population.

8.6 Renal Impairment

Prior to administration of gadobutrol, screen all patients for renal dysfunction by obtaining a history and/or laboratory tests [see Warnings and Precautions (5.2)]. No dosage adjustment is recommended for patients with renal impairment.

Gadobutrol can be removed from the body by hemodialysis [see Warnings and Precautions (5.2) and Clinical Pharmacology (12.3)].

10 OVERDOSAGE

The maximum dose of gadobutrol tested in healthy volunteers, 1.5 mL/kg body weight (1.5 mmol/kg; 15 times the recommended dose), was tolerated in a manner similar to lower doses. Gadobutrol can be removed by hemodialysis [see Use in Specific Populations (8.6) and Clinical Pharmacology (12.3)].

11 DESCRIPTION

Gadobutrol injection is a paramagnetic macrocyclic contrast agent administered intravenously for magnetic resonance imaging. The chemical name for gadobutrol is 10–[(1SR,2RS)–2,3–dihydroxy–1–hydroxymethylpropyl]–1,4,7,10– tetraazacyclododecane–1,4,7–triacetic acid, gadolinium complex. Gadobutrol has a molecular formula of C18H31GdN4O9 and a molecular weight of 604.72.

Gadobutrol injection is a sterile, clear, colorless to pale yellow solution containing 604.72 mg (1.0 mmol) of gadobutrol per mL as the active ingredient with 0.513 mg of calcobutrol sodium, 1.211 mg of trometamol, hydrochloric acid (for pH adjustment) and water for injection.

Gadobutrol injection contains no preservatives.

The main physicochemical properties of gadobutrol injection (1 mmol/mL solution for injection) are listed below:

Density (g/mL at 37°C) | 1.3
Osmolarity at 37°C (mOsm/L solution) | 1117
Osmolality at 37°C (mOsm/kg H2O) | 1603
Viscosity at 37°C (mPa·s) | 4.96
pH | 6.6 to 8

The thermodynamic stability constants for gadobutrol (log Ktherm and log Kcond at pH 7.4) are 21.8 and 15.3, respectively.

12 CLINICAL PHARMACOLOGY

12.1 Mechanism of Action

In MRI, visualization of normal and pathological tissue depends in part on variations in the radiofrequency signal intensity that occurs with:

- Differences in proton density
- Differences of the spin-lattice or longitudinal relaxation times (T1)
- Differences in the spin-spin or transverse relaxation time (T2)

When placed in a magnetic field, gadobutrol shortens the T1 and T2 relaxation times. The extent of decrease of T1 and T2 relaxation times, and therefore the amount of signal enhancement obtained from gadobutrol, is based upon several factors including the concentration of gadobutrol in the tissue, the field strength of the MRI system, and the relative ratio of the longitudinal and transverse relaxation times. At the recommended dose, the T1 shortening effect is observed with greatest sensitivity in T1-weighted magnetic resonance sequences. In T2*-weighted sequences the induction of local magnetic field inhomogeneities by the large magnetic moment of gadolinium and at high concentrations (during bolus injection) leads to a signal decrease.

12.2 Pharmacodynamics

Gadobutrol leads to distinct shortening of the relaxation times even in low concentrations. At pH 7, 37°C and 1.5 T, the relaxivity (r1) - determined from the influence on the relaxation times (T1) of protons in plasma - is 5.2 L/(mmol·sec) and the relaxivity (r2) - determined from the influence on the relaxation times (T2) - is 6.1 L/(mmol·sec). These relaxivities display only slight dependence on the strength of the magnetic field. The T1 shortening effect of paramagnetic contrast agents is dependent on concentration and r1 relaxivity (see Table 3). This may improve tissue visualization.

Table 3: Relaxivity (r1) of Gadolinium Chelates at 1.5 T
Gadolinium-Chelate | r1 (L·mmol ^-1 ·s ^-1)
Gadobenate | 6.3
Gadobutrol | 5.2
Gadodiamide | 4.3
Gadofosveset | 16
Gadopentetate | 4.1
Gadoterate | 3.6
Gadoteridol | 4.1
Gadoversetamide | 4.7
Gadoxetate | 6.9
r1 relaxivity in plasma at 37°C

Compared to 0.5 molar gadolinium-based contrast agents, the higher concentration of gadobutrol results in half the volume of administration and a more compact contrast bolus injection. At the site of imaging, the relative height and width of the time intensity curve for gadobutrol varies as a function of imaging location and multiple patient, injection, and device-specific factors.

Gadobutrol is a water-soluble, hydrophilic compound with a partition coefficient between n-butanol and buffer at pH 7.6 of about 0.006.

12.3 Pharmacokinetics

Distribution

After intravenous administration, gadobutrol is rapidly distributed in the extracellular space. After a gadobutrol dose of 0.1 mmol/kg body weight, an average level of 0.59 mmol gadobutrol/L was measured in plasma 2 minutes after the injection and 0.3 mmol gadobutrol/L 60 minutes after the injection. Gadobutrol does not display any particular protein binding. Following GBCA administration, gadolinium is present for months or years in brain, bone, skin, and other organs [see Warnings and Precautions (5.5)].

Metabolism

Gadobutrol is not metabolized.

Elimination

Values for AUC, body weight normalized plasma clearance and half-life are given in Table 4, below.

Gadobutrol is excreted in an unchanged form via the kidneys. In healthy subjects, renal clearance of gadobutrol is 1.1 to 1.7 mL/(min∙kg) and thus comparable to the renal clearance of inulin, confirming that gadobutrol is eliminated by glomerular filtration.

Within two hours after intravenous administration more than 50% and within 12 hours more than 90% of the given dose is eliminated via the urine. Extra-renal elimination is negligible.

Specific Populations

Gender

Gender has no clinically relevant effect on the pharmacokinetics of gadobutrol.

Geriatric

A single intravenous dose of 0.1 mmol/kg gadobutrol was administered to 15 elderly and 16 non-elderly subjects. AUC was slightly higher and clearance slightly lower in elderly subjects as compared to non-elderly subjects [see Use in Specific Populations (8.5)].

Pediatric

The pharmacokinetics of gadobutrol were evaluated in two studies in a total of 130 patients age 2 to less than 18 years and in 43 patients less than 2 years of age (including term neonates). Patients received a single intravenous dose of 0.1 mmol/kg of gadobutrol. The pharmacokinetic profile of gadobutrol in pediatric patients is similar to that in adults, resulting in similar values for AUC, body weight normalized plasma clearance, as well as elimination half-life. Approximately 99% (median value) of the dose was recovered in urine within 6 hours (this information was derived from the 2 to less than 18 year old age group).

Table 4: Pharmacokinetics by Age Group (Median [Range])
 | 0 to < 2 years N=43 | 2 to 6 years N=45 | 7 to 11 years N=39 | 12 to < 18 years N=46 | Adults N=93
AUC (μmolxh/L) | 781 [513, 1891] | 846 [412, 1331] | 1025 [623, 2285] | 1237 [946, 2211] | 1072 [667, 1992]
CL (L/h/kg) | 0.128 [0.053, 0.195] | 0.119 [0.08, 0.215] | 0.099 [0.043, 0.165] | 0.081 [0.046, 0.103] | 0.094 [0.051, 0.150]
t1/2 (h) | 2.91 [1.60, 12.4] | 1.91 [1.04, 2.70] | 1.66 [0.91, 2.71] | 1.68 [1.31, 2.48] | 1.80 [1.20, 6.55]
C20 (μmol/L) | 367 [280, 427] | 421 [369, 673] | 462 [392, 760] | 511 [387, 1077] | 441 [281, 829]

Renal Impairment

In patients with impaired renal function, the serum half-life of gadobutrol is prolonged and correlated with the reduction in creatinine clearance.

After intravenous injection of 0.1 mmol gadobutrol/kg body weight, the elimination half-life was 5.8 ± 2.4 hours in mild to moderately impaired patients (80 > CLCR > 30 mL/min) and 17.6 ± 6.2 hours in severely impaired patients not on dialysis (CLCR< 30 mL/min). The mean AUC of gadobutrol in patients with normal renal function was 1.1 ± 0.1 mmol∙h/L, compared to 4.0 ± 1.8 mmol∙h/L in patients with mild to moderate renal impairment and 11.5 ± 4.3 mmol∙h/L in patients with severe renal impairment.

Complete recovery in the urine was seen in patients with mild or moderate renal impairment within 72 hours. In patients with severely impaired renal function about 80% of the administered dose was recovered in the urine within 5 days. For patients receiving hemodialysis, physicians may consider the prompt initiation of hemodialysis following the administration of gadobutrol in order to enhance the contrast agent's elimination. Sixty-eight percent (68%) of gadobutrol is removed from the body after the first dialysis, 94% after the second dialysis, and 98% after the third dialysis session. [see Warnings and Precautions (5.2) and Use in Specific Populations (8.6).]

13 NONCLINICAL TOXICOLOGY

13.1 Carcinogenesis, Mutagenesis, Impairment of Fertility

No carcinogenicity studies of gadobutrol have been conducted.

Gadobutrol was not mutagenic in in vitro reverse mutation tests in bacteria, in the HGPRT (hypoxanthine-guanine phosphoribosyl transferase) test using cultured Chinese hamster V79 cells, or in chromosome aberration tests in human peripheral blood lymphocytes, and was negative in an in vivo micronucleus test in mice after intravenous injection of 0.5 mmol/kg.

Gadobutrol had no effect on fertility and general reproductive performance of male and female rats when given in doses 12.2 times the human equivalent dose (based on body surface area).

13.2 Animal Toxicology and/or Pharmacology

Local intolerance reactions, including moderate irritation associated with infiltration of inflammatory cells was observed after paravenous administration to rabbits, suggesting the possibility of occurrence of local irritation if the contrast medium leaks around veins in a clinical setting [see Warnings and Precautions (5.7)].

14 CLINICAL STUDIES

14.1 MRI of the CNS

Patients referred for MRI of the central nervous system with contrast were enrolled in two clinical trials that evaluated the visualization characteristics of lesions. In both studies, patients underwent a baseline, pre-contrast MRI prior to administration of gadobutrol at a dose of 0.1 mmol/kg, followed by a post-contrast MRI. In Study A, patients also underwent an MRI before and after the administration of gadoteridol. The studies were designed to demonstrate superiority of gadobutrol MRI to non-contrast MRI for lesion visualization. For both studies, pre-contrast and pre-plus-post contrast images (paired images) were independently evaluated by three readers for contrast enhancement and border delineation using a scale of 1 to 4, and for internal morphology using a scale of 1 to 3 (Table 5). Lesion counting was also performed to demonstrate non-inferiority of paired gadobutrol image sets to pre-contrast MRI. Readers were blinded to clinical information.

Table 5: Primary Endpoint Visualization Scoring System
Score | Visualization Characteristics
Score | Contrast Enhancement | Border Delineation | Internal Morphology
1 | None | None | Poorly visible
2 | Weak | Moderate | Moderately visible
3 | Clear | Clear but incomplete | Sufficiently visible
4 | Clear and bright | Clear and complete | N/A

Efficacy was determined in 657 subjects. The average age was 49 years (range 18 to 85 years) and 42% were male. The ethnic representations were 39% Caucasian, 4% Black, 16% Hispanic, 38% Asian, and 3% of other ethnic groups.

Table 6 shows a comparison of visualization results between paired images and pre-contrast images. Gadobutrol provided a statistically significant improvement for each of the three lesion visualization parameters when averaged across three independent readers for each study.

Table 6: Visualization Endpoint Results of Central Nervous System Adult MRI Studies with 0.1 mmol/kg Gadobutrol
Endpoint | Study A N=336 |  |  |  | Study B N=321
Endpoint | Pre-contrast | Paired | Difference^1 | Pre-contrast | Paired | Difference
Contrast Enhancement | 0.97 | 2.26 | 1.29^2 | 0.93 | 2.86 | 1.94^2
Border Delineation | 1.98 | 2.58 | 0.60^2 | 1.92 | 2.94 | 1.02^2
Internal Morphology | 1.32 | 1.93 | 0.60^2 | 1.57 | 2.35 | 0.78^2
Average # Lesions Detected | 8.08 | 8.25 | 0.17^4 | 2.65 | 2.97 | 0.32^3
^1 Difference of means = (paired mean) – (pre-contrast mean)
^2 p<0.001
^3 Met noninferiority margin of -0.35
^4 Did not meet noninferiority margin of -0.35

Performances of gadobutrol and gadoteridol for visualization parameters were similar. Regarding the number of lesions detected, Study B met the prespecified noninferiority margin of -0.35 for paired read versus pre-contrast read while in Study A, gadobutrol and gadoteridol did not.

For the visualization endpoints contrast enhancement, border delineation, and internal morphology, the percentage of patients scoring higher for paired images compared to pre-contrast images ranged from 93% to 99% for Study A, and 95% to 97% for Study B. For both studies, the mean number of lesions detected on paired images exceeded that of the pre-contrast images; 37% for Study A and 24% for Study B. There were 29% and 11% of subjects in which the pre-contrast images detected more lesions for Study A and Study B, respectively.

The percentage of patients whose average reader mean score changed by ≤ 0, up to 1, up to 2, and ≥ 2 scoring categories presented in Table 5 is shown in Table 7. The categorical improvement of (≤ 0) represents higher (< 0) or identical (= 0) scores for the pre-contrast read, the categories with scores > 0 represent the magnitude of improvement seen for the paired read.

Table 7: Primary Endpoint Visualization Categorical Improvement for Average Reader
 | Study A N=336 |  |  |  | Study B N=321
Endpoint | Categorical Improvement (Paired – Pre-Contrast) % |  |  |  | Categorical Improvement (Paired – Pre-Contrast) %
 | ≤ 0 | > 0 to < 1 | 1 to < 2 | ≥ 2 | ≤ 0 | > 0 to < 1 | 1 to < 2 | ≥ 2
Contrast Enhancement | 1 | 30 | 55 | 13 | 3 | 6 | 34 | 57
Border Delineation | 7 | 73 | 18 | 1 | 5 | 38 | 51 | 5
Internal Morphology | 4 | 79 | 17 | 0 | 5 | 61 | 33 | 1

For both studies, the improvement of visualization endpoints in paired gadobutrol images compared to pre-contrast images resulted in improved assessment of normal and abnormal CNS anatomy.

Pediatric Patients

Two studies in 44 pediatric patients age younger than 2 years and 135 pediatric patients age 2 to less than 18 years with CNS and non-CNS lesions supported extrapolation of adult CNS efficacy findings. For example, comparing pre vs paired pre- and post-contrast images, investigators selected the best of four descriptors under the heading, “Visualization of lesion-internal morphology (lesion characterization) or homogeneity of vessel enhancement” for 27/44 (62% = pre) vs 43/44 (98% = paired) MR images from patients age 0 to less than 2 years and 106/135 (78% = pre) vs 108/135 (80% = paired) MR images from patients age 2 to less than 18 years.

14.2 MRI of the Breast

Patients with recently diagnosed breast cancer were enrolled in two identical clinical trials to evaluate the ability of gadobutrol to assess the presence and extent of malignant breast disease prior to surgery. Patients underwent non-contrast breast MRI (BMR) prior to gadobutrol (0.1 mmol/kg) breast MRI. BMR images and gadobutrol BMR (combined contrast plus non-contrast) images were independently evaluated in each study by three readers blinded to clinical information. In separate reading sessions the BMR images and gadobutrol BMR images were also interpreted together with X-ray mammography images (XRM).

The studies evaluated 787 patients: Study 1 enrolled 390 women with an average age of 56 years, 74% were white, 25% Asian, 0.5% black, and 0.5% other; Study 2 enrolled 396 women and 1 man with an average age of 57 years, 71% were white, 24% Asian, 3% black, and 2% other.

The readers assessed 5 regions per breast for the presence of malignancy using each reading modality. The readings were compared to an independent standard of truth (SoT) consisting of histopathology for all regions where excisions were made and tissue evaluated. XRM plus ultrasound was used for all other regions.

The assessment of malignant disease was performed using a region based within-subject sensitivity. Sensitivity for each reading modality was defined as the mean of the percentage of malignant breast regions correctly interpreted for each subject. The within-subject sensitivity of gadobutrol BMR was superior to that of BMR. The lower bound of the 95% Confidence Interval (CI) for the difference in within-subject sensitivity ranged from 19% to 42% for Study 1 and from 12% to 27% for Study 2. The within-subject sensitivity for gadobutrol BMR and BMR as well as for gadobutrol BMR plus XRM and BMR plus XRM is presented in Table 8.

Table 8: Sensitivity of Gadobutrol BMR for Detection of Malignant Breast Disease
 |  | Study 1 |  |  |  |  | Study 2
 |  | Sensitivity (%) N=388 Patients |  |  |  |  | Sensitivity (%) N=390 Patients
Reader | BMR | BMR + | Gadobutrol | Gadobutrol | Reader | BMR | BMR | Gadobutrol | Gadobutrol
 |  | XRM | BMR | BMR |  |  | + XRM | BMR | BMR
 |  |  |  | +XRM |  |  |  |  | +XRM
1 | 37 | 71 | 83 | 84 | 4 | 73 | 83 | 87 | 90
2 | 49 | 76 | 80 | 83 | 5 | 57 | 81 | 89 | 90
3 | 63 | 75 | 87 | 87 | 6 | 55 | 80 | 86 | 88

Specificity was defined as the percentage of non-malignant breasts correctly identified as non-malignant. The lower limit of the 95% confidence interval for specificity of gadobutrol BMR was greater than 80% for 5 of 6 readers. (Table 9)

Table 9: Specificity of Gadobutrol BMR in Non-Malignant Breasts
 | Study 1 |  |  | Study 2
 | Specificity (%) N=372 Patients |  |  | Specificity (%) N=367 Patients
Reader | Gadobutrol BMR | Lower Limit 95% CI | Reader | Gadobutrol BMR | Lower Limit 95% CI
1 | 86 | 82 | 4 | 92 | 89
2 | 95 | 93 | 5 | 84 | 80
3 | 89 | 85 | 6 | 83 | 79

Three additional readers in each study read XRM alone. For these readers over both studies, sensitivity ranged from 68% to 73% and specificity in non-malignant breasts ranged from 86% to 94%.

In breasts with malignancy, a false positive detection rate was calculated as the percentage of subjects for which the readers assessed a region as malignant which could not be verified by SoT. The false positive detection rates for gadobutrol BMR ranged from 39% to 53% (95% CI Upper Bounds ranged from 44% to 58%).

14.3 MRA

Patients with known or suspected disease of the supra-aortic arteries (for evaluation up to but excluding the basilar artery) were enrolled in Study C, and patients with known or suspected disease of the renal arteries were enrolled in Study D. In both studies, non-contrast, 2D time-of-flight (ToF) magnetic resonance angiography (MRA) was performed prior to gadobutrol MRA using a single intravenous injection of 0.1 mmol/kg. The injection rate of 1.5 mL/second was selected to extend the injection duration to at least half of the imaging duration. Imaging was performed with parallel-channel, 1.5T MRI devices and an automatic bolus tracking technique to trigger the image acquisition following gadobutrol administration using elliptically encoded, T1-weighted, 3D gradient-echo image acquisition and single breath hold. Three central readers blinded to clinical information interpreted the ToF and gadobutrol MRA images. Three additional central readers interpreted separately acquired computed tomographic angiography (CTA) images, which were used as the standard of reference (SoR) in each study.

The studies included 749 subjects: 457 were evaluated in Study C, with an average age of 68 (range 25 to 93); 64% were male; 80% white, 28% black, and 16% Asian. An additional 292 subjects were evaluated in Study D, with an average age of 55 (range 18 to 88); 54% were male; 68% white, 7% black, and 22% Asian.

Efficacy was evaluated based on anatomical visualization and performance for distinguishing between normal and abnormal anatomy. The visualization metric depended on whether readers selected, “Yes, it can be visualized along its entire length...” when responding to the question, “Is this segment assessable?”. Twenty-one segments in Study C and six segments in Study D were presented per subject to each reader. The performance metrics, sensitivity and specificity, depended on digital caliper-based quantitation of arterial narrowing in visualized, non-occluded, abnormal-appearing segments. Significant stenosis was defined as at least 70% in Study C and 50% in Study D. Performance of gadobutrol MRA compared to ToF MRA was calculated using an imputation method for non-visualized segments by assigning them as a 50% match with SoR and a 50% mismatch. Performance of gadobutrol MRA compared to a pre-specified threshold of 50% was calculated after excluding non-visualized segments. Measurement variability and visualization of accessory renal arteries was also evaluated.

Results were analyzed for each of the three central readers.

Table 10: Visualization, Sensitivity, Specificity
STUDY C: SUPRA-AORTIC ARTERIES (457 patients) Performance at the segment level 9597^1 segments of which 158^1 were positive for stenosis by SoR^2
 | VISUALIZATION (%) |  |  | SENSITIVITY (%) |  |  | SPECIFICITY (%)
READER | GAD MRA | ToF MRA | GAD − ToF (CI^3) | GAD MRA | ToF MRA | GAD − ToF (CI^4) | GAD MRA | ToF MRA | GAD − ToF (CI^4)
1 | 88 | 24 | 64 (61, 67) | 60 | 54 | 6 (-4, 14) | 92 | 62 | 30 (29, 32)
2 | 95 | 75 | 20 (18, 21) | 60 | 54 | 6 (-3, 14) | 95 | 85 | 10 (9, 11)
3 | 97 | 82 | 15 (13, 17) | 58 | 55 | 3 (-4, 11) | 97 | 89 | 8 (7, 9)
STUDY D: RENAL ARTERIES (292 patients) Performance at the segment level 1752^1 segments of which 133^1 were positive for stenosis by SoR^2
4 | 98 | 82 | 16 (13, 20) | 52 | 51 | 1 (-9, 11) | 94 | 83 | 11 (9, 14)
5 | 96 | 72 | 24 (21, 28) | 54 | 39 | 15 (6, 24) | 95 | 85 | 10 (8, 12)
6 | 96 | 78 | 17 (14, 21) | 53 | 50 | 3 (-6, 12) | 94 | 81 | 13 (11, 16)
^1Number of segments varied between readers; number for majority-reader shown.
^2Standard of Reference based on aggregate interpretation of three central CTA readers.
^395.1/95% (Study C/D) confidence interval for two-sided comparison.
^490.1/90% (Study C/D) confidence interval for one-sided comparison against non-inferiority margin of -7.5.
GAD MRA = Post-contrast Gadobutrol Magnetic Resonance Angiography, ToF = Non-contrast 2D-Time of Flight.

For all three supra-aortic artery readers in Study C, the lower bound of confidence for the sensitivity of gadobutrol MRA did not exceed 54%. For all three renal artery readers in Study D, the lower bound of confidence for the sensitivity of gadobutrol MRA did not exceed 46%.

Measurement Variability

For both MRA and CTA, readers varied in the quantity of narrowing they assigned to the same arterial segments. Table 11 shows the percentage of patients in whom the measurement range was 30% or greater for the left or right internal carotid and proximal renal artery segments. There were approximately four measurements per patient segment, one from the site and three from the central readers. Measurement variability was high for both CTA and MRA, but numerically lower for gadobutrol compared to non-contrast ToF MRA.

Table 11: Percent of Patients with Range ≥ 30%, ≥ 50%, ≥ 70% for Measurement of Stenoses and Normal Vessel Diameters
 | Internal Carotid |  |  |  | Proximal Main Renal
 | N | ≥ 30% | ≥ 50% | ≥ 70% | N | ≥ 30% | ≥ 50% | ≥ 70%
CTA | 456 | 40 | 11 | 4 | 292 | 59 | 33 | 9
ToF MRA | 443 | 55 | 22 | 9 | 270 | 44 | 22 | 9
Gadobutrol MRA | 454 | 47 | 13 | 4 | 286 | 34 | 14 | 4

Visualization of Accessory Renal Arteries for Surgical Planning and Renal Donor Evaluation (Study D only)

Of 1752 main arteries visualized by the central CTA readers, 266 (15%) were also associated with positive visualization of at least one accessory (duplicate) artery. With the central MRA readers, the comparable rates were 232 of 1752 (13%) for gadobutrol MRA compared to 53 of 1752 (3%) for ToF MRA.

14.4 Cardiac MRI

Two studies similar in design, Study E and Study F, evaluated the sensitivity and specificity of gadobutrol cardiac MRI (CMRI) for detection of coronary artery disease (CAD) in adult patients with known or suspected CAD. Patients were excluded from study if they had a history of coronary artery bypass grafting, or if it was known in advance that they were unable to hold their breath, or had atrial fibrillation or other arrhythmia likely to prevent electrocardiogram-gated CMRI. The studies were multi-center, open-label, and evaluated 764 subjects for efficacy: 376 in Study E, with an average age of 59 (range 20 to 84); 69% male; 74% white, 1% black, and 25% Asian; and 388 subjects in Study F, with an average age of 59 (range 23 to 82); 61% male; 67% white, 17% black, and 12% Asian.

All subjects underwent dynamic first-pass gadobutrol imaging during vasodilator stress, followed ~10 minutes later by dynamic first-pass gadobutrol imaging at rest, followed ~5 minutes later with imaging during a period of gradual gadobutrol washout from the myocardium (late gadolinium enhancement, LGE). Imaging was performed on 1.5 T or 3.0 T MRI devices equipped with multichannel surface coils to support accelerated acquisitions with parallel imaging, T1-weighted, 2D gradient-echo, dynamic acquisition of perfusion with at least 3 slices per heartbeat. Gadobutrol was administered intravenously at a rate of ~4 mL/second as two separate bolus injections (0.05 mmol/kg each), the first at peak pharmacologic stress (~3 minutes after start of ongoing adenosine infusion, or immediately after completion of regadenoson administration, at approved doses). No additional gadobutrol was administered for LGE imaging.

Images were read by three independent readers blinded to clinical information. Reader detection of CAD depended on visually detecting defective perfusion or scar on gadobutrol CMRI (stress, rest, LGE) imaging. Quantitative coronary angiography (QCA) was used to measure intraluminal narrowing and served as the standard of reference (SoR).

Computed tomographic angiography (CTA) was used as the SoR if disease could be unequivocally excluded, and no coronary angiography (CA) was available. The left ventricular myocardium was divided into six regions. Readers provided per-region (CMRI, CTA) and per-artery (QCA) interpretations for each subject. Subject-level endpoints reflected each subject's most abnormal localized finding.

The sensitivity results for gadobutrol CMRI to detect CAD defined as either maximum stenosis ≥ 50% or ≥ 70% by QCA are presented in Table 12. For each reader, sensitivity of gadobutrol CMRI larger than 60% can be concluded if the lower 95% confidence limit of the sensitivity estimate exceeds the pre-specified threshold of 60%.

Table 12: Sensitivity (%) of Gadobutrol CMRI for Detection of CAD in Patients with Maximum Stenosis* of ≥ 50% and ≥ 70%
 | Study E |  | Study F
 | ≥ 50% N=141 | ≥ 70% N=108 | ≥ 50% N=150 | ≥ 70% N=105
Reader 1** | 77 (69, 83)*** | 90 (83, 95) | 65 (57, 72) | 77 (68, 85)
Reader 2** | 65 (57, 73) | 80 (71, 87) | 56 (48, 64) | 71 (62, 80)
Reader 3** | 65 (56, 72) | 79 (70, 86) | 61 (53, 69) | 76 (67, 84)
* Stenosis determined by Quantitative Coronary Angiography (QCA)
** CMRI images were assessed by six independent blinded readers, three in each study.
*** The bolded value represents the lower limit of the 95% confidence interval, which is compared to a pre-specified threshold of 60% for evaluation of sensitivity.

The specificity results for gadobutrol CMRI to detect CAD defined as either maximum stenosis ≥ 50% or ≥ 70% by QCA are presented in Table 13. For each reader, specificity of gadobutrol CMRI larger than 55% can be concluded if the lower 95% confidence limit of the specificity estimate exceeds the pre-specified threshold of 55%.

Table 13: Specificity (%) of Gadobutrol CMRI for Exclusion of CAD in Patients with Maximum Stenosis* of ≥ 50% and ≥ 70%
 | Study E |  | Study F
 | ≥ 50% N=235 | ≥ 70% N=268 | ≥ 50% N=239 | ≥ 70% N=283
Reader 1** | 85 (80, 89)*** | 83 (78, 87) | 85 (80, 90) | 82 (77, 86)
Reader 2** | 92 (88, 95) | 91 (87, 94) | 89 (84, 92) | 87 (83, 91)
Reader 3** | 92 (88, 95) | 91 (87, 94) | 90 (85, 93) | 87 (82, 91)
* Stenosis determined by Quantitative Coronary Angiography (QCA)
** CMRI images were assessed by six independent blinded readers, three in each study.
*** The bolded value represents the lower limit of the 95% confidence interval, which is compared to a pre-specified threshold of 55% for evaluation of specificity.

In Study E, among the 33 patients with maximum stenosis by QCA between 50% and <70%, the proportion of gadobutrol-CMRI positive detections of CAD ranged from 15% to 33%. In Study F, among the 45 patients with maximum stenosis by QCA between 50% and < 70%, the proportion of gadobutrol-CMRI positive detections of CAD ranged from 20% to 35%. The results of gadobutrol-CMRI reads to detect CAD in patients with maximum stenosis between 50% and < 70% are summarized in Table 14.

Table 14: Gadobutrol-CMRI Detection of CAD in Patients with Maximum Stenosis* between 50% and < 70%
 | Study E (n=33) | Study F (n=45)
 | Gadobutrol-CMRI positive | Gadobutrol-CMRI positive
Reader 1** | 11 (33%) | 16 (35%)
Reader 2** | 5(15%) | 9 (20%)
Reader 3** | 6(18%) | 12 (26%)
* Stenosis determined by Quantitative Coronary Angiography (QCA).
**CMRI images were assessed by six independent blinded readers, three in each study.

Left Mainstem Stenosis (LMS)

The studies did not include sufficient numbers of subjects to characterize the performance of gadobutrol CMRI for detection of LMS, a subgroup at high risk from false negative reads. In Studies E and F, only three subjects had isolated LMS stenosis >50%. In two of the three cases, the CMRI was interpreted as normal by at least two of the three readers (false negative). Sixteen subjects had LMS stenosis >50% (including subjects with isolated LMS stenosis and subjects with LMS stenosis in addition to stenoses elsewhere). In five of these sixteen cases, the CMR was interpreted as normal by at least two of the three readers (false negative).

16 HOW SUPPLIED/STORAGE AND HANDLING

16.1 How Supplied

Gadobutrol injection is a sterile, clear and colorless to pale yellow solution containing 604.72 mg gadobutrol per mL (equivalent to 1 mmol gadobutrol per mL). Gadobutrol injection is supplied in the following Multiple-Dose container sizes:

Product Code | Unit of Sale | Each
287230 | NDC 65219-287-30 Packaged in cartons of 10. | NDC 65219-287-10 30 mL Imaging Bulk Package with rubber stopper.
287265 | NDC 65219-289-65 Packaged in cartons of 10. | NDC 65219-289-10 65 mL Imaging Bulk Package with rubber stopper.

16.2 Storage and Handling

Store at 25°C (77°F); excursions permitted to 15° to 30°C (59° to 86°F) [see USP Controlled Room Temperature].

Should freezing occur, gadobutrol injection should be brought to room temperature before use. If allowed to stand at room temperature, gadobutrol injection should return to a clear and colorless to pale yellow solution. Visually inspect gadobutrol injection for particulate matter and discoloration prior to administration. Do not use the solution if it is discolored, if particulate matter is present or if the container appears damaged.

17 PATIENT COUNSELING INFORMATION

- Advise the patient to read the FDA-approved patient labeling (Medication Guide).

Nephrogenic Systemic Fibrosis

Instruct patients to inform their physician if they:

- Have a history of kidney disease and/or liver disease, or
- Have recently received a GBCA

GBCAs increase the risk of NSF among patients with impaired elimination of drugs. To counsel patients at risk of NSF:

- Describe the clinical manifestation of NSF
- Describe procedures to screen for the detection of renal impairment

Instruct the patients to contact their physician if they develop signs or symptoms of NSF following gadobutrol injection administration, such as burning, itching, swelling, scaling, hardening and tightening of the skin; red or dark patches on the skin; stiffness in joints with trouble moving, bending or straightening the arms, hands, legs or feet; pain in the hip bones or ribs; or muscle weakness.

Common Adverse Reactions

Inform patients that they may experience:

- Reactions along the venous injection site, such as mild and transient burning or pain or feeling of warmth or coldness at the injection site
- Side effects of headache, nausea, abnormal taste and feeling hot

Acute Respiratory Distress Syndrome

- Advise patients that acute respiratory distress syndrome (ARDS) has occurred with gadobutrol injection. Inform patients on the symptoms of the observed ARDS cases, and instruct patients to inform their healthcare provider if they experience these symptoms [see Warnings and Precautions (5.4)].

General Precautions

Gadolinium Retention

- Advise patients that gadolinium is retained for months or years in brain, bone, skin, and other organs in patients with normal renal function. The clinical consequences of retention are unknown. Retention depends on multiple factors and is greater following administration of linear GBCAs than following administration of macrocyclic GBCAs [see Warnings and Precautions (5.5)].

Instruct patients receiving gadobutrol injection to inform their physician if they:

- Are pregnant or breastfeeding
- Have a history of allergic reaction to contrast media, bronchial asthma or allergic respiratory disorder

Manufactured for:

Lake Zurich, IL 60047

www.fresenius-kabi.com/us

Product of China
Revised: May 2025

451796C
26EUF04

MEDICATION GUIDE

Gadobutrol Injection
Gadobutrol (“gad” oh bue' trol)
Injection for intravenous use

What is the most important information I should know about gadobutrol injection?

- GBCAs like Gadobutrol injection may cause serious side effects including death, coma, encephalopathy, and seizures when it is given intrathecally (injection given into the spinal canal). It is not known if Gadobutrol injection is safe and effective with intrathecal use. Gadobutrol injection is not approved for this use.
- Gadobutrol injection contains a metal called gadolinium. Small amounts of gadolinium can stay in your body including the brain, bones, skin and other parts of your body for a long time (several months to years).
- It is not known how gadolinium may affect you, but so far, studies have not found harmful effects in patients with normal kidneys.
- Rarely, patients have reported pains, tiredness, and skin, muscle or bone ailments for a long time, but these symptoms have not been directly linked to gadolinium.
- There are different GBCAs that can be used for your MRI exam. The amount of gadolinium that stays in the body is different for different gadolinium medicines. Gadolinium stays in the body more after Omniscan or Optimark than after Eovist, Magnevist, or MultiHance. Gadolinium stays in the body the least after Dotarem, Gadobutrol injection, or ProHance.
- People who get many doses of gadolinium medicines, women who are pregnant and young children may be at increased risk from gadolinium staying in the body.
- Some people with kidney problems who get gadolinium medicines can develop a condition with severe thickening of the skin, muscles and other organs in the body (nephrogenic systemic fibrosis). Your healthcare provider should screen you to see how well your kidneys are working before you receive gadobutrol injection.

What is gadobutrol injection?

- Gadobutrol injection is a prescription medicine called a gadolinium-based contrast agent (GBCA). Gadobutrol injection, like other GBCAs, is injected into your vein and used with a magnetic resonance imaging (MRI) scanner.
- An MRI exam with a GBCA, including gadobutrol injection, helps your doctor to see problems better than an MRI exam without a GBCA.
- Your doctor has reviewed your medical records and has determined that you would benefit from using a GBCA with your MRI exam.

Do not receive gadobutrol injection if you have had a severe allergic reaction to gadobutrol injection.

Before receiving gadobutrol injection, tell your healthcare provider about all your medical conditions, including if you:

- have had any MRI procedures in the past where you received a GBCA. Your healthcare provider may ask you for more information including the dates of these MRI procedures.
- are pregnant or plan to become pregnant. It is not known if gadobutrol injection can harm your unborn baby. Talk to your healthcare provider about the possible risks to an unborn baby if a GBCA such as gadobutrol injection is received during pregnancy.
- have kidney problems, diabetes, or high blood pressure
- have had an allergic reaction to dyes (contrast agents) including GBCAs

What are the possible side effects of gadobutrol injection?

- See “What is the most important information I should know about gadobutrol injection?”
- Allergic reactions. Gadobutrol injection can cause allergic reactions that can sometimes be serious. Your healthcare provider will monitor you closely for symptoms of an allergic reaction.
- A serious lung problem called acute respiratory distress syndrome (ARDS). Call your healthcare provider right away if you have shortness of breath with or without a fever, trouble breathing, or a fast rate of breathing after receiving gadobutrol injection.

The most common side effects of gadobutrol injection include: headache, nausea, and dizziness.
These are not all the possible side effects of gadobutrol injection.
Call your doctor for medical advice about side effects. You may report side effects to FDA at 1-800-FDA-1088.

General information about the safe and effective use of gadobutrol injection.
Medicines are sometimes prescribed for purposes other than those listed in a Medication Guide. You can ask your healthcare provider for information about gadobutrol injection that is written for health professionals.

What are the ingredients in gadobutrol injection?
Active ingredient: gadobutrol
Inactive ingredients: calcobutrol sodium, trometamol, hydrochloric acid (for pH adjustment) and water for injection
Manufactured for:
Lake Zurich, IL 60047
www.fresenius-kabi.com/us
For more information, call Fresenius Kabi USA, LLC at 1-800-551-7176.

This Medication Guide has been approved by the U.S. Food and Drug Administration.

5/2025

26EUF04

451796C

PACKAGE LABEL

PRINCIPAL DISPLAY PANEL – 30 mmol/30 mL (1 mmol/mL) – Shelf Carton

Dose: 0.1 mL/kg

NDC 65219-287-30
Gadobutrol Injection
30 mmol/30 mL
(1 mmol/mL)

Imaging Bulk Package - Not for Direct Infusion

For Intravenous Use Only
Discard 24 hours after initial puncture
Dispense the enclosed Medication Guide to each patient.

PACKAGE LABEL

PRINCIPAL DISPLAY PANEL – 30 mmol/30 mL (1 mmol/mL) – Bottle Label

Dose: 0.1 mL/kg

NDC 65219-287-10
Gadobutrol
Injection
30 mmol/30 mL
(1 mmol/mL)

Imaging Bulk Package -
Not for Direct Infusion

For Intravenous Use Only
Multiple-Dose Bottle
Discard 24 hours after initial
puncture

Discard after ___ / ___ / ___
at ___ : ___

PACKAGE LABEL

PRINCIPAL DISPLAY PANEL – 65 mmol/65 mL (1 mmol/mL) – Shelf Carton

Dose: 0.1 mL/kg

NDC 65219-289-65
Gadobutrol Injection
65 mmol/65 mL
(1 mmol/mL)

Imaging Bulk Package - Not for Direct Infusion

For Intravenous Use Only
Discard 24 hours after initial puncture
Dispense the enclosed Medication Guide to each patient.

PACKAGE LABEL

PRINCIPAL DISPLAY PANEL – 65 mmol/65 mL (1 mmol/mL) – Bottle Label

Dose: 0.1 mL/kg

NDC 65219-289-10
Gadobutrol
Injection
65 mmol/65 mL
(1 mmol/mL)

Imaging Bulk Package -
Not for Direct Infusion

For Intravenous Use Only
Multiple-Dose Bottle
Discard 24 hours after initial puncture

Discard after ___ / ___ / ___ at ___ : ___